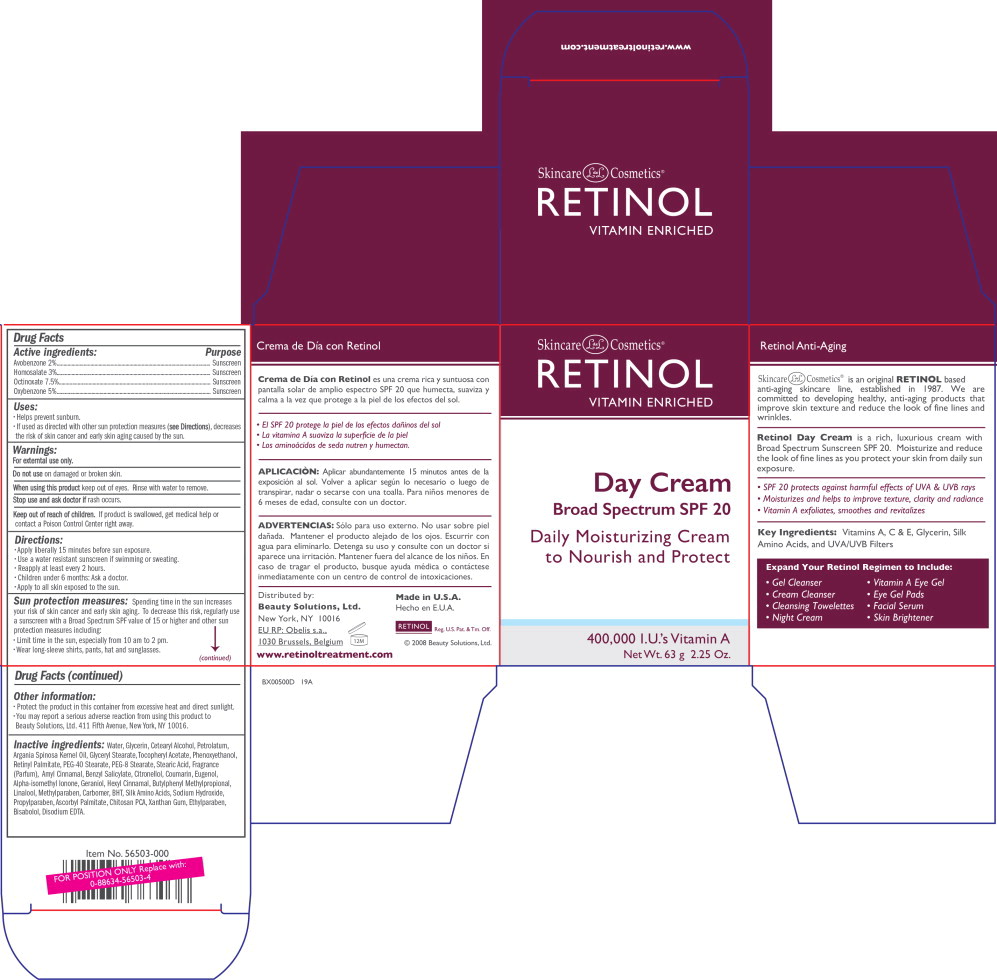 DRUG LABEL: Skincare LdeL Retinol 
NDC: 51117-001 | Form: CREAM
Manufacturer: Beauty Solutions, Ltd.

Category: otc | Type: HUMAN OTC DRUG LABEL
Date: 20240801

ACTIVE INGREDIENTS: Avobenzone
 20 mg/1 g; Homosalate
 30 mg/1 g; Oxybenzone
 50 mg/1 g; Octinoxate
 75 mg/1 g
INACTIVE INGREDIENTS: Water; Glycerin; Argan Oil; .Alpha.-Tocopherol Acetate; Levomenol; Cetostearyl Alcohol; Petrolatum; Glyceryl Monostearate; Phenoxyethanol; Methylparaben; Propylparaben; Ethylparaben; Vitamin A Palmitate; Peg-40 Stearate; Peg-8 Stearate; Stearic Acid; Sodium Hydroxide; CARBOMER INTERPOLYMER TYPE A (ALLYL SUCROSE CROSSLINKED); Amino Acids, Silk; BUTYLATED HYDROXYTOLUENE; Xanthan Gum; Edetate Disodium; Ascorbyl Palmitate; .Alpha.-Amylcinnamaldehyde; Benzyl Salicylate; .Beta.-Citronellol, (R)-; Coumarin; Eugenol; Isomethyl-.Alpha.-Ionone; Geraniol; .Alpha.-Hexylcinnamaldehyde; Butylphenyl Methylpropional; Linalool, (+/-)-

Drug Facts

Active ingredients:

Avobenzone 2%

Homosalate 3%

Octinoxate 7.5%

Oxybenzone 5%

Purpose

Sunscreen

Sunscreen

Sunscreen

Sunscreen

Uses:

- Helps prevent sunburn.
- If used as directed with other sun protection measures (see Directions), decreases the risk of skin cancer and early skin aging caused by the sun.

Warnings:

For external use only.

Do not use on damaged or broken skin.

When using this product keep out of eyes. Rinse with water to remove.

Stop use and ask doctor if rash occurs.

Keep out of reach of children. If product is swallowed, get medical help or contact a Poison Control Center right away.

Directions:

- Apply liberally 15 minutes before sun exposure.
- Use a water resistant sunscreen if swimming or sweating.
- Reapply at least every 2 hours.
- Children under 6 months: Ask a doctor.
- Apply to all skin exposed to the sun.

Sun protection measures: Spending time in the sun increases your risk of skin cancer and early skin aging. To decrease this risk, regularly use a sunscreen with a Broad Spectrum SPF value of 15 or higher and other sun protection measures including:

- Limit time in the sun, especially from 10 am to 2 pm.
- Wear long-sleeve shirts, pants, hat and sunglasses.

Other information:

- Protect the product in this container from excessive heat and direct sunlight.
- You may report a serious adverse reaction from using this product to Beauty Solutions, Ltd. 411 Fifth Avenue, New York, NY 10016.

Inactive ingredients:

Water, Glycerin, Cetearyl Alcohol, Petrolatum, Argania Spinosa Kernel Oil, Glyceryl Stearate, Tocopheryl Acetate, Phenoxyethanol, Retinyl Palmitate, PEG-40 Stearate, PEG-8 Stearate, Stearic Acid, Fragrance (Parfum), Amyl Cinnamal, Benzyl Salicylate, Citronellol, Coumarin, Eugenol, Alpha-isomethyl Ionone, Geraniol, Hexyl Cinnamal, Butylphenyl Methylpropional, Linalool, Methylparaben, Carbomer, BHT, Silk Amino Acids, Sodium Hydroxide, Propylparaben, Ascorbyl Palmitate, Chitosan PCA, Xanthan Gum, Ethylparaben, Bisabolol, Disodium EDTA.

Principal Display Panel - 63g Jar Carton

Skincare LdeL Cosmetics®
RETINOL

VITAMIN ENRICHED

Day Cream
Broad Spectrum SPF 20

Daily Moisturizing Cream
to Nourish and Protect

Net Wt. 63 g 2.25 Oz.